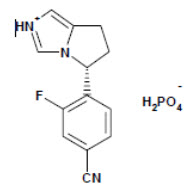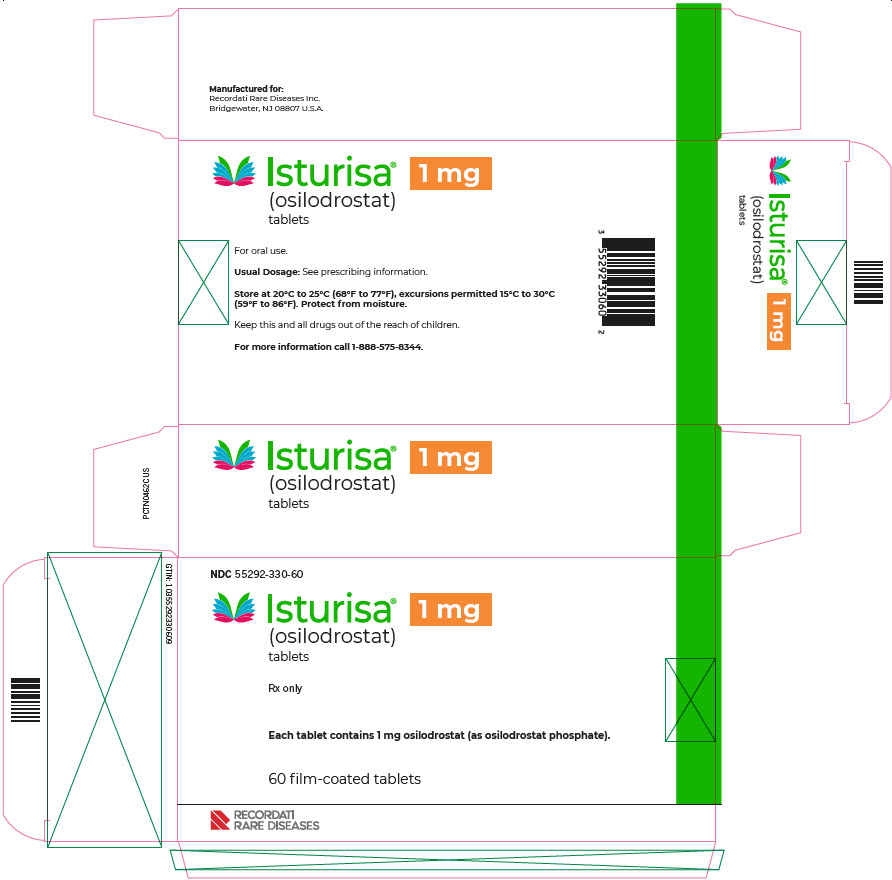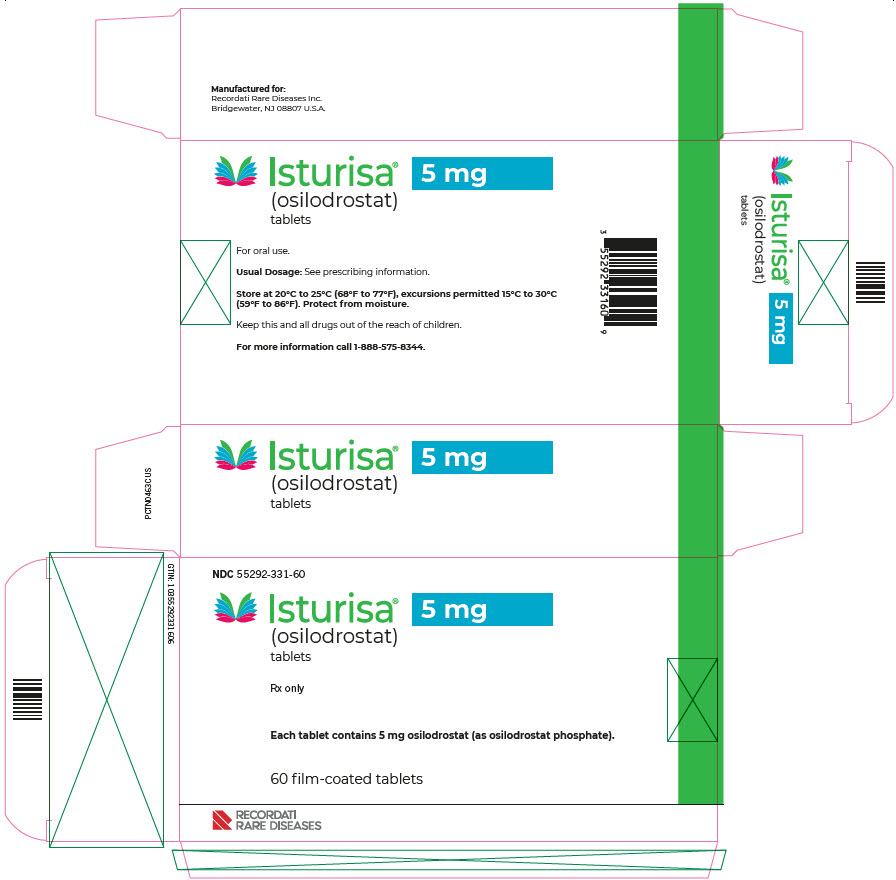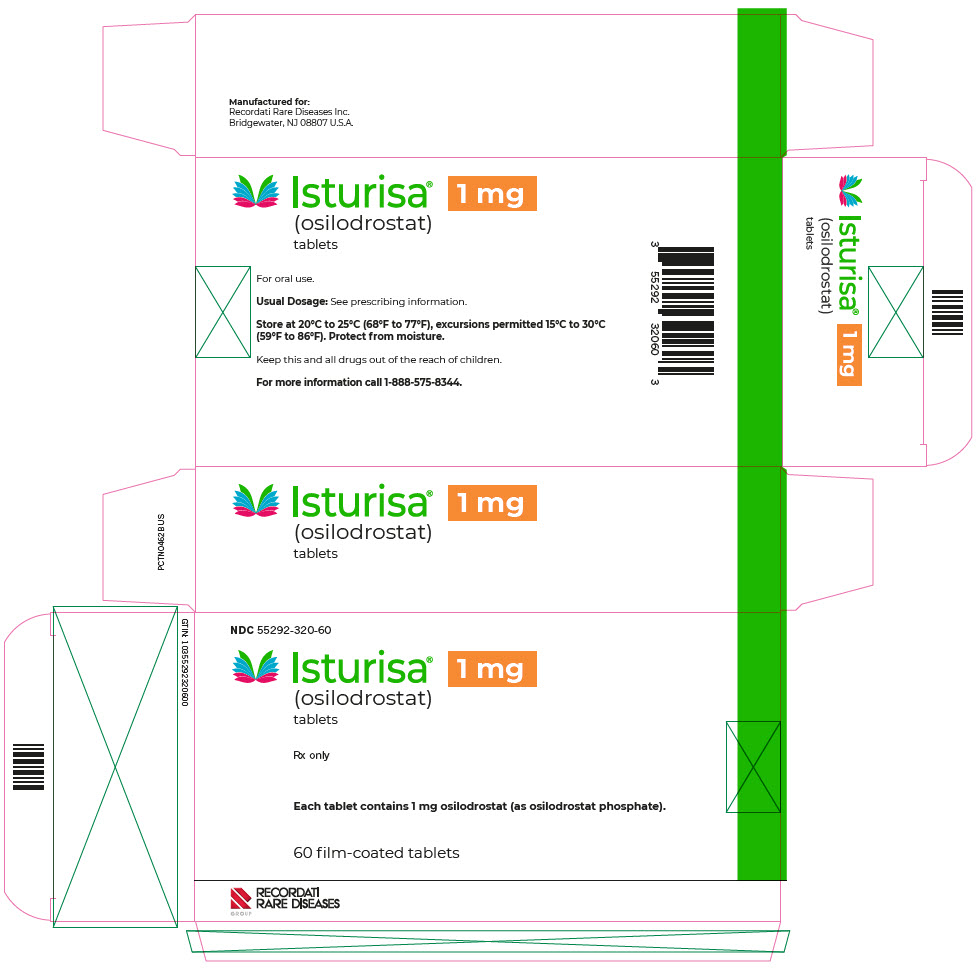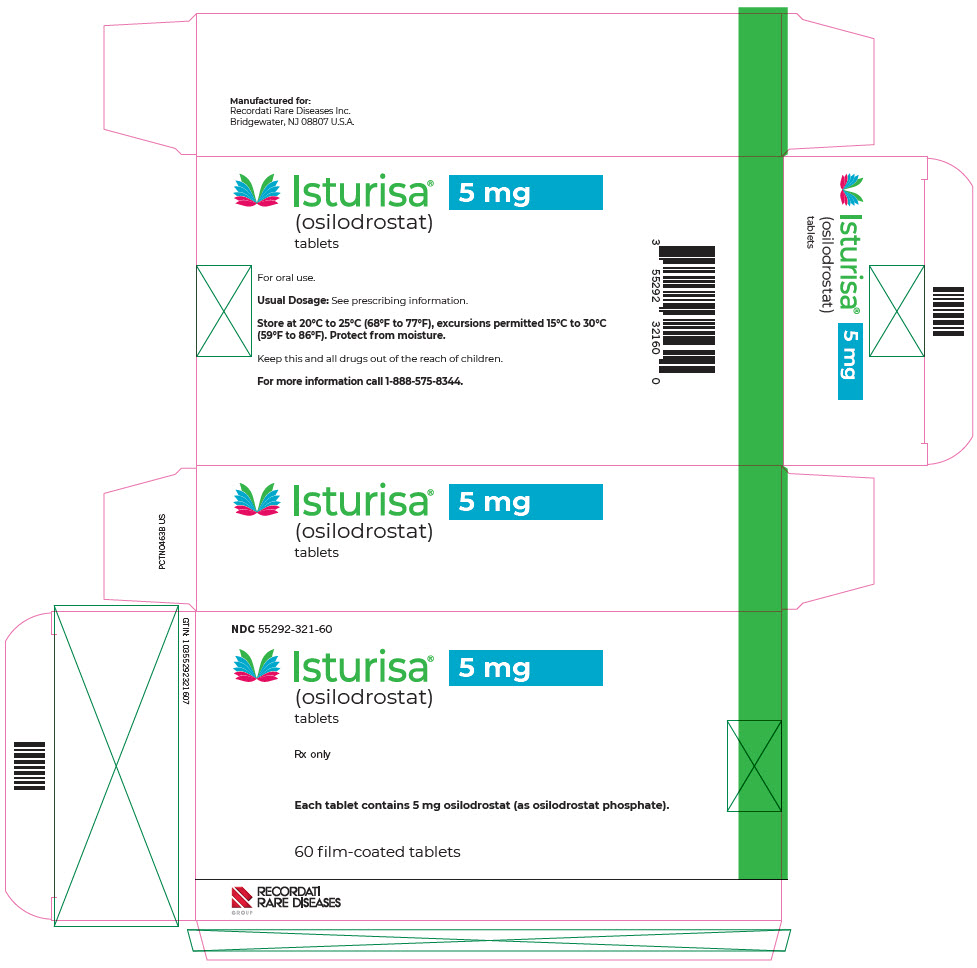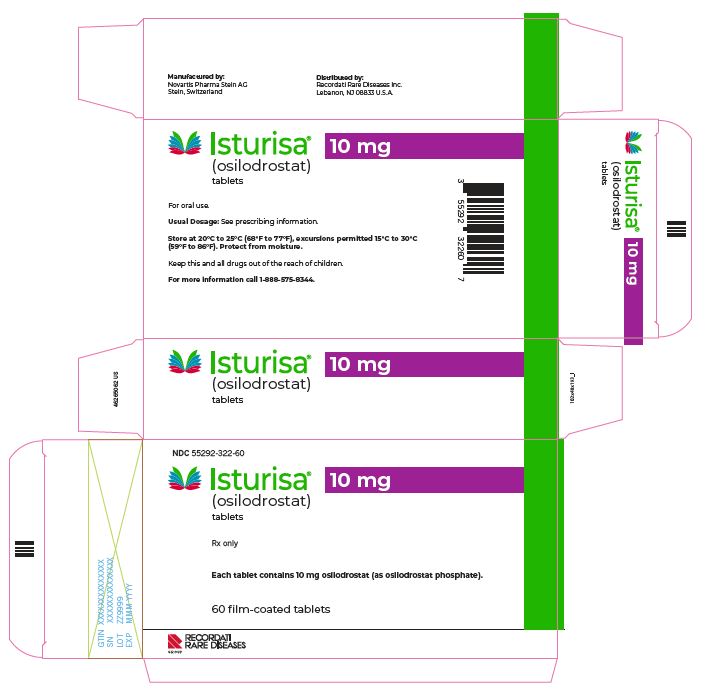 DRUG LABEL: Isturisa
NDC: 55292-330 | Form: TABLET, COATED
Manufacturer: Recordati Rare Diseases, Inc.
Category: prescription | Type: HUMAN PRESCRIPTION DRUG LABEL
Date: 20251118

ACTIVE INGREDIENTS: OSILODROSTAT PHOSPHATE 1 mg/1 1
INACTIVE INGREDIENTS: SILICON DIOXIDE; CROSCARMELLOSE SODIUM; MANNITOL; MICROCRYSTALLINE CELLULOSE; MAGNESIUM STEARATE; HYPROMELLOSE, UNSPECIFIED; TITANIUM DIOXIDE; FERRIC OXIDE YELLOW; FERRIC OXIDE RED; POLYETHYLENE GLYCOL 4000; TALC

HIGHLIGHTS OF PRESCRIBING INFORMATION

These highlights do not include all the information needed to use ISTURISA® safely and effectively. See full prescribing information for ISTURISA.
ISTURISA (osilodrostat) tablets, for oral use
Initial U.S. Approval: 2020

RECENT MAJOR CHANGES

Indications and Usage (1) | 04/2025

1 INDICATIONS AND USAGE

ISTURISA is a cortisol synthesis inhibitor indicated for the treatment of endogenous hypercortisolemia in adults with Cushing's syndrome for whom surgery is not an option or has not been curative (1)

2 DOSAGE AND ADMINISTRATION

- Correct hypokalemia and hypomagnesemia, and obtain baseline electrocardiogram prior to starting ISTURISA (2.1, 5.2, 5.3)
- Initiate dosage at 2 mg orally twice daily, with or without food (2.2)
- Titrate dosage by 1 mg to 2 mg twice daily, no more frequently than every 2 weeks based on rate of cortisol changes, individual tolerability and improvement in signs and symptoms (2.2)
- Maximum recommended dosage is 30 mg twice daily (2.2)
- See Full Prescribing Information for complete titration, laboratory, and dosage modification recommendations (2.1, 2.2, 2.3)
- Patients with Hepatic Impairment:
  - Child-Pugh B: Recommended starting dose is 1 mg twice daily (2.5, 8.7)
  - Child-Pugh C: Recommended starting dose is 1 mg once daily in the evening (2.5, 8.7)

3 DOSAGE FORMS AND STRENGTHS

Tablets: 1 mg and 5 mg (3)

4 CONTRAINDICATIONS

None (4)

5 WARNINGS AND PRECAUTIONS

- Hypocortisolism: Monitor patients closely for hypocortisolism and potentially life-threatening adrenal insufficiency. Dosage reduction or interruption may be necessary. After interruption or discontinuation of ISTURISA, cortisol suppression may persist and patients should be regularly monitored (5.1)
- QTc Prolongation: Perform electrocardiogram in all patients Use with caution in patients with risk factors for QTc prolongation (5.2)
- Elevations in Adrenal Hormone Precursors and Androgens: Monitor for hypokalemia, worsening of hypertension, edema, and hirsutism (5.3)

6 ADVERSE REACTIONS

Most common adverse reactions (incidence > 20%) are adrenal insufficiency, fatigue, nausea, headache, edema, decreased appetite, arthralgia, myalgia, and diarrhea (6)

To report SUSPECTED ADVERSE REACTIONS, contact Recordati Rare Diseases Inc. at 1-888-575-8344 or FDA at 1-800-FDA-1088 or www.fda.gov/medwatch.

7 DRUG INTERACTIONS

- CYP3A4 Inhibitor: Reduce the dose of ISTURISA by half with concomitant use of a strong CYP3A4 inhibitor (7.1)
- CYP3A4 and CYP2B6 Inducers: An increase of ISTURISA dosage may be needed if ISTURISA is used concomitantly with strong CYP3A4 and CYP2B6 inducers. A reduction in ISTURISA dosage may be needed if strong CYP3A4 and CYP2B6 inducers are discontinued while using ISTURISA (7.1)

8 USE IN SPECIFIC POPULATIONS

- Lactation: Breastfeeding is not recommended during treatment with ISTURISA and for at least one week after treatment (8.2)

FULL PRESCRIBING INFORMATION

1 INDICATIONS AND USAGE

ISTURISA is indicated for the treatment of endogenous hypercortisolemia in adults with Cushing's syndrome for whom surgery is not an option or has not been curative.

2 DOSAGE AND ADMINISTRATION

2.1 Laboratory Testing Prior to ISTURISA Initiation

- Correct hypokalemia and hypomagnesemia prior to starting ISTURISA [see Warnings and Precautions (5.2, 5.3)].
- Obtain baseline electrocardiogram (ECG). Repeat ECG within one week after treatment initiation, and as clinically indicated thereafter [see Warnings and Precautions (5.2)].

2.2 Recommended Dosage, Titration, and Monitoring

- Initiate dosing at 2 mg orally twice daily, with or without food.
- Initially, titrate the dosage by 1 mg to 2 mg twice daily, no more frequently than every 2 weeks based on the rate of cortisol changes, individual tolerability and improvement in signs and symptoms of Cushing's syndrome. If a patient tolerates ISTURISA dosage of 10 mg twice daily and continues to have elevated 24-hour urine free cortisol (UFC) levels above upper normal limit, the dosage can be titrated further by 5 mg twice daily every 2 weeks. Monitor cortisol levels from at least two 24-hour urine free cortisol collections every 1 to 2 weeks until adequate clinical response is maintained.
- The maintenance dosage of ISTURISA is individualized and determined by titration based on cortisol levels and patient's signs and symptoms.
- The maintenance dosage varied between 2 mg and 7 mg twice daily in clinical trials. The maximum recommended maintenance dosage of ISTURISA is 30 mg twice daily [see Clinical Studies (14)].
- Once the maintenance dosage is achieved, monitor cortisol levels at least every 1 to 2 months or as indicated.

2.3 Dosage Interruptions and Modifications

- Decrease or temporarily discontinue ISTURISA if urine free cortisol levels fall below the target range, there is a rapid decrease in cortisol levels, and/or patients report symptoms of hypocortisolism. If necessary, glucocorticoid replacement therapy should be initiated.
- Stop ISTURISA and administer exogenous glucocorticoid replacement therapy if serum or plasma cortisol levels are below target range and patients have symptoms of adrenal insufficiency [see Warnings and Precautions (5.1)].
- If treatment is interrupted, re-initiate ISTURISA at a lower dose when cortisol levels are within target ranges and patient symptoms have been resolved.

2.4 Recommended Dosage and Monitoring in Patients with Renal Impairment

- No dose adjustment is required for patients with renal impairment. Use caution in interpreting urine free cortisol levels in patients with moderate to severe renal impairment, due to reduced urine free cortisol excretion [see Clinical Pharmacology (12.3)].

2.5 Recommended Dosage and Monitoring in Patients with Hepatic Impairment

- For patients with moderate hepatic impairment (Child-Pugh B), the recommended starting dose is 1 mg twice daily. For patients with severe hepatic impairment (Child-Pugh C), the recommended starting dose is 1 mg once daily in the evening.
- No dose adjustment is required for patients with mild hepatic impairment (Child-Pugh A).
- More frequent monitoring of adrenal function may be required during dose titration in all patients with hepatic impairment [see Clinical Pharmacology (12.3)].

2.6 Missed Dose

If a dose of ISTURISA is missed, the patient should take their next dose at the regularly scheduled time.

3 DOSAGE FORMS AND STRENGTHS

ISTURISA is available as:

- 1 mg tablets: Pale yellow, unscored, round, biconvex with beveled edge tablet, debossed "1" on one side.
- 5 mg tablets: Yellow, unscored, round, biconvex with beveled edge tablet, debossed "5" on one side.

4 CONTRAINDICATIONS

None.

5 WARNINGS AND PRECAUTIONS

5.1 Hypocortisolism

ISTURISA lowers cortisol levels and can lead to hypocortisolism and sometimes life-threatening adrenal insufficiency. Lowering of cortisol can cause nausea, vomiting, fatigue, abdominal pain, loss of appetite, dizziness. Significant lowering of serum cortisol may result in hypotension, abnormal electrolyte levels, and hypoglycemia [see Adverse Reactions (6)].

Hypocortisolism can occur at any time during ISTURISA treatment. Evaluate patients for precipitating causes of hypocortisolism (infection, physical stress, etc.). Monitor 24-hour urine free cortisol, serum or plasma cortisol, and patient's signs and symptoms periodically during ISTURISA treatment.

Decrease or temporarily discontinue ISTURISA if urine free cortisol levels fall below the target range, there is a rapid decrease in cortisol levels, and/or patients report symptoms of hypocortisolism. Stop ISTURISA and administer exogenous glucocorticoid replacement therapy if serum or plasma cortisol levels are below target range and patients have symptoms of adrenal insufficiency. After interruption or discontinuation of ISTURISA, cortisol suppression may persist beyond the 4 hour half-life. Monitor patients regularly and re-initiate ISTURISA at a lower dose when urine free cortisol, serum or plasma cortisol levels are within target range, and/or patient symptoms have resolved.

Educate patients on the symptoms associated with hypocortisolism and advise them to contact a healthcare provider if they occur.

5.2 QTc Prolongation

ISTURISA is associated with a dose-dependent QT interval prolongation (maximum mean estimated QTcF increase of up to 5.3 ms at 30 mg), which may cause cardiac arrhythmias [see Adverse Reactions (6), Clinical Pharmacology (12.2)].

Perform an ECG to obtain a baseline QTc interval measurement prior to initiating therapy with ISTURISA and monitor for an effect on the QTc interval thereafter. Correct hypokalemia and/or hypomagnesemia prior to ISTURISA initiation and monitor periodically during treatment with ISTURISA. Correct electrolyte abnormalities if indicated. Consider temporary discontinuation of ISTURISA in the case of an increase in QTc interval > 480 ms.

Use caution in patients with risk factors for QT prolongation, (such as congenital long QT syndrome, congestive heart failure, bradyarrhythmias, uncorrected electrolyte abnormalities, and concomitant medications known to prolong the QT interval) and consider more frequent ECG monitoring.

5.3 Elevations in Adrenal Hormone Precursors and Androgens

ISTURISA blocks cortisol synthesis and may increase circulating levels of cortisol and aldosterone precursors (11-deoxy cortisol and 11-deoxycorticosterone) and androgens.

Elevated 11-deoxycorticosterone levels may activate mineralocorticoid receptors and cause hypokalemia, edema and hypertension [see Adverse Reactions (6)]. Hypokalemia should be corrected prior to initiating ISTURISA. Monitor patients treated with ISTURISA for hypokalemia, worsening of hypertension and edema. ISTURISA-induced hypokalemia should be treated with intravenous or oral potassium supplementation based on event severity. If hypokalemia persists despite potassium supplementation, consider adding mineralocorticoid antagonists. ISTURISA dose reduction or discontinuation may be necessary.

Accumulation of androgens may lead to hirsutism, hypertrichosis and acne (in females). Inform patients of the symptoms associated with hyperandrogenism and advise them to contact a healthcare provider if they occur.

6 ADVERSE REACTIONS

Clinically significant adverse reactions that appear in other sections of the labeling include:

- Hypocortisolism [see Warnings and Precautions (5.1)]
- QT Prolongation [see Warnings and Precautions (5.2)]
- Elevations in Adrenal Hormone Precursors and Androgens [see Warnings and Precautions (5.3)]

6.1 Clinical Trials Experience

Because clinical trials are conducted under widely varying conditions, adverse reaction rates observed in the clinical trials of a drug cannot be directly compared to rates in clinical trials of another drug and may not reflect the rates observed in practice.

The safety of ISTURISA was evaluated in two clinical trials in adults with Cushings disease. Study 1 (NCT02180217) was a 4-period, multicenter study with a 12-week open-label titration period, 12-week open-label maintenance period, 8-week double-blind, placebo-controlled period, and 14 to 24-week open label treatment period in 137 patients with Cushing's disease. Study 2 (NCT02697734) was a 2-period, multicenter study with a 12-week randomized, double-blind, placebo-controlled period and a 36-week open-label treatment period in 74 patients with Cushing's disease [see Clinical Studies (14)].

Study 1

The adverse reactions that occurred with frequency higher than 10% during the core 48-week period are shown in Table 1.

Table 1: Adverse Reactions With a Frequency of More Than 10% in 48-week Clinical Study 1 in Adults with Cushing's Disease
Adverse Reaction Type | (N = 137) %
Adrenal insufficiency [Adrenal insufficiency includes glucocorticoid deficiency, adrenocortical insufficiency acute, steroid withdrawal syndrome, cortisol free urine decreased, cortisol decreased. One-third of the subjects with this event had low cortisol levels indicative of Adrenal Insufficiency. The majority of subjects had normal cortisol levels suggesting a cortisol withdrawal syndrome.] | 43.1
Fatigue [Fatigue includes lethargy, asthenia.] | 38.7
Nausea | 37.2
Headache [Headache includes head discomfort.] | 30.7
Edema [Edema includes edema peripheral, generalized edema, localized edema.] | 21.2
Nasopharyngitis | 19.7
Vomiting | 19
Arthralgia | 17.5
Back pain | 15.3
Rash [Rash includes rash erythematous, rash generalized, rash maculopapular, rash papular.] | 15.3
Diarrhea | 14.6
Blood corticotrophin increased | 13.9
Dizziness [Dizziness includes dizziness postural.] | 13.9
Abdominal pain [Abdominal pain includes abdominal pain upper, abdominal discomfort] | 13.1
Hypokalemia [Hypokalemia includes blood potassium decreased.] | 12.4
Myalgia | 12.4
Decreased appetite | 11.7
Hormone level abnormal | 11.7
Hypotension [Hypotension includes orthostatic hypotension, blood pressure decreased, blood pressure diastolic decreased, blood pressure systolic decreased.] | 11.7
Urinary tract infection | 11.7
Blood testosterone increased | 10.9
Pyrexia | 10.9
Anemia | 10.2
Cough | 10.2
Hypertension | 10.2
Influenza | 10.2

Other notable adverse reactions which occurred with a frequency less than 10% were: hirsutism (9.5%), acne (8.8%), dyspepsia (8%), insomnia (8%), anxiety (7.3%), depression (7.3%), gastroenteritis (7.3%), malaise (6.6%), tachycardia (6.6%), alopecia (5.8%), transaminases increased (4.4%), electrocardiogram QT prolongation (3.6%), and syncope (1.5%).

Description of Select Adverse Reactions from the Core 48-week Period of Study 1

Gastrointestinal Disorders

Gastrointestinal disorders, predominantly nausea, vomiting, diarrhea and abdominal pain were reported in 69% of patients. In many cases, the episodes were of short duration (1-2 days) and the severity was mild to moderate.

Hypocortisolism

Hypocortisolism was reported at a rate of 31% up to 12 weeks, and 18% from Weeks 12 to 26. The majority of cases were manageable by reducing the dose of ISTURISA and/or adding low-dose, short-term glucocorticoid therapy.

Changes in Pituitary Tumor Volume

An increase in the pituitary corticotroph tumor volume by greater than 20% from baseline was observed in 21/137 (15%) patients, while a decrease in tumor volume by greater than 20% from baseline was observed in 24/137 (18%) patients at Week 48. Eight patients discontinued because of an increase in tumor volume. There was no correlation between tumor volume increase and increase in adrenocorticotrophic hormone (ACTH). There was no specific pattern of timing of the tumor volume increase and no relationship with the total and the last dose of ISTURISA used in the study.

QTc Interval Prolongation

Adverse reactions of QT prolongation and clinically relevant ECG findings were reported. Five (4%) patients had an event of QT prolongation, 3 (2%) patients had a QTcF increase of > 60ms from baseline, and 18 (13%) had a new QTcF value of > 450ms [see Clinical Pharmacology (12.2)].

Accumulation of Adrenal Hormone Precursors

CYP11B1 inhibition by ISTURISA is associated with adrenal steroid precursor accumulation and testosterone increases [see Warnings and Precautions (5.3)].

The incidence of adverse reactions potentially related to accumulation of adrenal hormone precursors was 42%. Hypertension and hypokalemia were the most common adrenal hormone precursor-related adverse reactions and occurred in 14% of patients and 17% of patients, respectively; edema was reported in 7% of patients, elevated blood pressure in 15% of patients. All cases of hypokalemia responded to treatment with potassium supplementation and/or mineralocorticoid antagonist therapy (e.g., spironolactone). One patient discontinued the study because of hypokalemia. In male patients testosterone levels generally increased but remained within normal limits; all patients were asymptomatic with no values above upper limit of normal (ULN) at last available value. In female patients, mean testosterone levels increased above the normal range from baseline and reversed when treatment was interrupted. The testosterone increase was associated with mild to moderate cases of hirsutism (12%) or acne (11%) in a subset of female patients.

Other Abnormal Laboratory Findings

Decreased Absolute Neutrophil Count

Of the 137 patients from the 48-week study 1, 18 patients had at least one measured absolute neutrophil count below the normal limit, 2 patients had an adverse reaction of neutropenia. No concomitant infections and/or fever were reported in patients with decreased absolute neutrophil count.

Elevated Liver Function Tests

Liver enzyme elevations in patients treated with ISTURISA were infrequent, typically mild and reversed spontaneously or following dose adjustment. Most liver abnormal parameters occurred during the dose-titration period and no patients discontinued ISTURISA drug due to abnormal liver chemistry parameters. Five (4%) patients had ALT or AST > 3 × ULN during the 48-week clinical study.

Study 2

The adverse reactions that occurred with frequency higher than 10% and greater than placebo during the 12-week placebo controlled period are shown in Table 2.

Table 2: Adverse Reactions With a Frequency of More Than 10% and Greater Than Placebo in the 12-week Placebo Controlled Period of Clinical Study 2 in Adults with Cushing's Disease
Adverse Reaction Type | ISTURISA (N = 48) % | Placebo (N=25) %
Decreased appetite | 38 | 16
Arthralgia | 35 | 12
Nausea | 31 | 12
Fatigue [fatigue includes asthenia, fatigue, and malaise] | 29 | 16
Myalgia [myalgia includes myalgia and fibromyalgia] | 23 | 4
Diarrhea | 21 | 0
Dizziness | 19 | 16
Adrenal insufficiency | 15 | 0
Tachycardia [tachycardia includes tachycardia and sinus tachycardia] | 15 | 0
Nasopharyngitis [nasopharyngitis includes upper respiratory tract infection, nasopharyngitis, and pharyngitis] | 15 | 4
Hypotension [hypotension includes hypotension and orthostatic hypotension] | 15 | 0
Pruritus | 13 | 0
Abdominal pain [abdominal pain includes abdominal pain, abdominal pain upper, and gastrointestinal pain] | 13 | 4
Renal and urinary tract infection [renal and urinary tract infection includes urinary tract infection and cystitis] | 13 | 0
Peripheral edema [peripheral edema includes edema peripheral and peripheral swelling] | 10 | 4
Viral infection [viral infection includes Influenza, conjunctivitis viral, Dengue fever, and oral herpes] | 10 | 0
Vomiting | 10 | 0
Blood testosterone increased | 10 | 0

Description of Selected Adverse Reactions from the 12-week Placebo-Controlled Period of Study 2

Hypocortisolism

Hypocortisolism was reported at a rate of 15% in ISTURISA arm and no subjects in placebo arm. The majority of cases were manageable by interrupting/reducing the dose of ISTURISA and/or adding low-dose, short-term glucocorticoid therapy.

QTc Interval Prolongation

One (2%) patient in ISTURISA arm had a new QTcF value of > 450ms versus none in placebo arm.

Accumulation of Adrenal Hormone Precursors

CYP11B1 inhibition by ISTURISA is associated with adrenal steroid precursor accumulation and testosterone increases [see Warnings and Precautions (5.3)].

The incidence of adverse reactions potentially related to accumulation of adrenal hormone precursors was 44% in ISTURISA arm and 36% in placebo arm. Hypertension, blood testosterone increase, peripheral edema, acne and hypokalemia were the most common adrenal hormone precursor-related adverse reactions and occurred in 17% 10%, 10%, 4% and 2% of patients in ISTURISA arm, and in 32%, 0%, 4%, 0% and 0% of patients in the placebo arm. Most cases of hypokalemia responded to treatment with potassium supplementation and/or mineralocorticoid antagonist therapy (e.g., spironolactone). One patient discontinued the study because of hypokalemia.

Other Abnormal Laboratory Findings

Decreased Absolute Neutrophil Count

Three (6%) patients in ISTURISA arm had at least one measured absolute neutrophil count below the normal limit and one (2%) of these was classified as Grade 3 by Common Terminology Criteria for Adverse Events (CTCAEs) grading. No patients in placebo arm had absolute neutrophil count below normal limit.

Elevated Liver Function Tests

Liver enzyme elevations in patients treated with ISTURISA were infrequent, typically mild and reversed spontaneously. No patient had concurrent increases in AST, ALT and total bilirubin and/or ALP. No patient met the criteria for Hy's Law. Two (4%) patients in ISTURISA arm versus none in placebo arm had ALT or AST > 3 × ULN.

6.2 Postmarketing Experience

Additional adverse reactions have been identified during postapproval use of ISTURISA. Because these reactions are reported voluntarily from a population of uncertain size, it is generally not possible to reliably estimate their frequency or establish a causal relationship to drug exposure.

- Neutropenia associated with fever and infection

7 DRUG INTERACTIONS

7.1 Effect of Other Drugs on ISTURISA

The effect of other drugs on ISTURISA can be found in Table 3.

Table 3: Effect of Other Drugs on ISTURISA
CYP3A4 Inhibitors
Clinical Impact: | Concomitant use of ISTURISA with a strong CYP3A4 inhibitor (e.g., itraconazole, clarithromycin) may cause an increase in osilodrostat concentration and may increase the risk of ISTURISA-related adverse reactions [see Clinical Pharmacology (12.3)].
Intervention: | Reduce the dose of ISTURISA by half with concomitant use of a strong CYP3A4 inhibitor.
CYP3A4 and CYP2B6 Inducers
Clinical Impact: | Concomitant use of ISTURISA with strong CYP3A4 and/or CYP2B6 inducers (e.g., carbamazepine, rifampin, phenobarbital) may cause a decrease in osilodrostat concentration and may reduce the efficacy of ISTURISA [see Clinical Pharmacology (12.3)]. Discontinuation of strong CYP3A4 and/or CYP2B6 inducers while using ISTURISA may cause an increase in osilodrostat concentration and may increase the risk of ISTURISA-related adverse reactions [see Clinical Pharmacology (12.3)].
Intervention: | During concomitant use of ISTURISA with strong CYP3A4 and CYP2B6 inducers, monitor cortisol concentration and patient's signs and symptoms. An increase in ISTURISA dosage may be needed. Upon discontinuation of strong CYP3A4 and CYP2B6 inducers during ISTURISA treatment, monitor cortisol concentration and patient's signs and symptoms. A reduction in ISTURISA dosage may be needed.

7.2 Effect of ISTURISA on Other Drugs

ISTURISA should be used with caution when coadministered with CYP1A2 and CYP2C19 substrates with a narrow therapeutic index, such as theophylline, tizanidine, and S-mephenytoin [see Clinical Pharmacology (12.3)].

8 USE IN SPECIFIC POPULATIONS

8.1 Pregnancy

Risk Summary

There are no available data on osilodrostat use in pregnant women to evaluate for a drug-associated risk of major birth defects, miscarriage, or adverse maternal or fetal outcomes. There are risks to the mother and fetus associated with active Cushing's Syndrome during pregnancy (see Clinical Considerations).

No adverse developmental outcomes were observed in reproduction studies in pregnant rats and rabbits when exposed to osilodrostat during organogenesis at doses that produced maternal exposures of 7 and 0.5-times the 30 mg twice daily maximum clinical dose, by AUC. In rabbits, exposures associated with maternal toxicity at 7-times the maximum clinical dose resulted in decreased fetal viability. No adverse developmental outcomes were observed in a pre- and postnatal development study with administration of osilodrostat to pregnant rats from organogenesis through lactation at 8-times the 30 mg twice daily maximum clinical dose (see Data).

The estimated background risk of major birth defects and miscarriage for the indicated population is unknown. In the U.S. general population, the estimated background risk of major birth defects and miscarriage in clinically recognized pregnancies is 2%-4% and 15%-20%, respectively.

Clinical Considerations

Disease-Associated Maternal and/or Embryo/Fetal Risk

Active Cushing Syndrome during pregnancy has been associated with an increased risk of maternal and fetal morbidity and mortality (including gestational diabetes, gestational hypertension, pre-eclampsia, maternal death, miscarriage, fetal loss, and preterm birth).

Data

Animal Data

Osilodrostat administered to pregnant Wistar Han rats from gestation day 6-17 at doses of 0.5, 5, 50 mg/kg did not adversely affect embryo-fetal development up to 5 mg/kg (8-times the 30mg twice daily maximum clinical dose, by AUC). Maternal toxicity, increased embryonic and fetal deaths, decreased fetal weights, and malformations occurred at 50 mg/kg (118-times the maximum clinical dose, by AUC).

Osilodrostat administered to pregnant New Zealand rabbits from gestation day 7-20 at doses of 3, 10, and 30 mg/kg did not adversely affect embryo-fetal development at 3mg/kg (0.5-times the 30 mg twice daily maximum clinical dose, by AUC). Maternal toxicity, increased embryo resorption and decreased fetal viability was observed at ≥ 10mg/kg (7-times the maximum clinical dose, by AUC).

Osilodrostat administered to Wistar Han rats from gestation day 6 through lactation day 20 at doses of 1, 5, and 20 mg/kg did not adversely impact behavioral, developmental, or reproductive parameters up to 5 mg/kg (~ 8 times the 30 mg twice daily maximum clinical dose, by AUC). Delayed parturition and dystocia in maternal rats and decreased pup survival were observed at 20 mg/kg (43-times the maximum clinical dose, by AUC).

8.2 Lactation

Risk Summary

There are no available data on the presence of osilodrostat in human or animal milk, the effects on the breastfed infant, or the effects on milk production. Because of the potential for serious adverse reactions (such as adrenal insufficiency) in the breastfed infant, advise patients that breastfeeding is not recommended during treatment with ISTURISA and for one week after the final dose.

8.4 Pediatric Use

The safety and effectiveness of ISTURISA in pediatric patients have not been established.

8.5 Geriatric Use

Of the 167 patients in clinical trials with ISTURISA, 10 (6%) were 65 years and older. There were no patients above 75 years of age. Based on the available data on the use of ISTURISA in patients older than 65 years, no dosage adjustment is required [see Clinical Pharmacology (12.3)].

8.6 Renal Impairment

No dosage adjustment of ISTURISA in patients with impaired renal function is required [see Dosage and Administration (2.4), Clinical Pharmacology (12.3)]. In patients with moderate to severe renal impairment, UFC levels should be interpreted with caution due to reduced UFC excretion.

8.7 Hepatic Impairment

Dosage adjustment is not required in patients with mild hepatic impairment (Child-Pugh A) but is required for patients with moderately impaired hepatic function (Child-Pugh B) and for patients with severe hepatic impairment (Child-Pugh C) [see Dosage and Administration (2.3), Clinical Pharmacology (12.3)]. More frequent monitoring of adrenal function may be required during dose titration in all patients with hepatic impairment.

10 OVERDOSAGE

Overdosage may result in severe hypocortisolism. Signs and symptoms suggestive of hypocortisolism may include nausea, vomiting, fatigue, low blood pressure, abdominal pain, loss of appetite, dizziness, and syncope.

In case of suspected overdosage, ISTURISA should be temporarily discontinued, cortisol levels should be checked, and if necessary, corticosteroid supplementation should be initiated. Close surveillance may be necessary, including monitoring of the QT interval, blood pressure, glucose, fluid, and electrolyte until the patient's condition is stable.

11 DESCRIPTION

ISTURISA (osilodrostat) is a cortisol synthesis inhibitor.

The chemical name of osilodrostat is 4-[(5R)-6,7-Dihydro-5H-pyrrolo[1,2-c]imidazol-5-yl]-3-fluorobenzonitrile dihydrogen phosphate.

Molecular formula of osilodrostat salt (phosphate) form on anhydrous basis is: (C13H11FN3) (H2PO4). Relative molecular mass of osilodrostat phosphate salt form is 325.24 g/mol.

ISTURISA tablets for oral administration contains 1 mg or 5 mg of osilodrostat equivalent to 1.4 mg or 7.2 mg of osilodrostat phosphate respectively, and the following inactive ingredients: colloidal silicon dioxide, croscarmellose sodium, mannitol, microcrystalline cellulose, and magnesium stearate. The film coat is composed of hypromellose, titanium dioxide, ferric oxide (yellow), ferric oxide (red) (1 mg only), polyethylene glycol 4000, and talc.

12 CLINICAL PHARMACOLOGY

12.1 Mechanism of Action

Osilodrostat is a cortisol synthesis inhibitor. It inhibits 11beta-hydroxylase (CYP11B1), the enzyme responsible for the final step of cortisol biosynthesis in the adrenal gland. In a Chinese hamster lung cell line V79-4 that overexpresses human CYP11B1, adrenodoxin and adrenodoxin reductase, osilodrostat inhibited the activity of human CYP11B1 dose-dependently with IC50 values of 2.5 ± 0.1 nM (n = 4).

12.2 Pharmacodynamics

A dose dependent increase was observed in 11-deoxycortisol, the cortisol precursor, and ACTH levels in patients with Cushing's disease.

Cardiac Electrophysiology

A thorough QT study in 86 male and female healthy volunteers showed a maximum mean placebo-corrected QTcF interval increase of 1.73 ms [90% confidence interval (CI): 0.15, 3.31] at a 10 mg dose, and 25.38 ms (90% CI: 23.53, 27.22) at a 150 mg dose (up to 2.5 times the maximum recommended dosage) [see Warnings and Precautions (5.2)].

The predicted mean placebo-corrected QTcF change from baseline at the highest recommended dose in clinical practice (30 mg twice daily) was estimated as 5.3 ms (90% CI: 4.2, 6.5), based on an interpolation of the data from the thorough QT Study and population PK analysis [see Warnings and Precautions (5.2)].

12.3 Pharmacokinetics

Absorption

Osilodrostat is absorbed with a time of maximum observed concentration (Tmax) of approximately 1 hour. Exposure (AUCinf and Cmax) slightly increases over dose-proportionally within the therapeutic dose range of 1 mg to 30 mg.

Effect of Food

In a healthy volunteer study (N = 20), subjects administered with a single, 30 mg oral dose of ISTURISA film-coated tablets with a high-fat meal resulted in reduction of AUC by 11% and Cmax by 21%, respectively. The median Tmax was delayed from 1 to 2.5 hours. These changes are not considered to be clinically significant, therefore ISTURISA can be administered with or without food.

Distribution

The median apparent volume of distribution of osilodrostat is approximately 100 L. Protein binding is low (36.4%). The osilodrostat blood-to-plasma concentration ratio is 0.85.

Elimination

The elimination half-life of osilodrostat is approximately 4 hours.

In an absorption, distribution, metabolism, and excretion study, the majority of the radioactivity dose of osilodrostat is eliminated in the urine (mean: 90.6% of administered dose) with only a minor amount eliminated in the feces (1.58% of dose). The low percentage of the dose eliminated in the urine as unchanged osilodrostat (5.2%) indicates that metabolism is the major clearance pathway in humans.

Metabolism

Multiple CYP enzymes (i.e., CYP3A4, CYP2B6, and CYP2D6) and UDP-glucuronosyltransferases contribute to osilodrostat metabolism and no single enzyme contributes greater than 25% to the total clearance. The metabolites are not expected to contribute to the pharmacological effect of osilodrostat.

Specific Populations

Age and gender have no significant impact on osilodrostat exposure in adults.

Race/Ethnicity

The relative bioavailability in Asian patients is approximately 20% higher compared to that of non-Asian, along with higher Tmax and Cmax, compared to other ethnicities. However, the difference is not clinically significant.

Patients with Renal Impairment

Osilodrostat exposure was similar in the three renal function groups [normal, severe, and end stage renal disease (ESRD) groups] and thus a study was not conducted in mild and moderate renal impairment groups. The results showed that the PK of osilodrostat was not influenced by varying degrees of renal impairment to any clinically significant extent [see Dosage and Administration (2.4), Use in Specific Populations (8.6)].

Patients with Hepatic Impairment

There was a trend of increasing AUCinf to osilodrostat in moderate and severe hepatic impaired subjects (geo-mean ratios are 1.44 and 2.66, respectively) as compared to normal subjects. Exposures (Cmax and AUC) of osilodrostat in the mild hepatic impairment group were similar to those in the normal group [see Dosage and Administration (2.5), Use in Specific Populations (8.7)].

Drug Interaction

In a healthy volunteer study (N = 20) using a single dose of osilodrostat (50 mg) and a probe drugs cocktail, osilodrostat showed inhibition potential on CYP1A2, CYP2C19, CYP2D6, and CYP3A4/5 isozymes with 2.5-, 1.9-, 1.5- and 1.5-fold increase in caffeine, omeprazole, dextromethorphan, and midazolam exposure, respectively [see Drug Interactions (7.1), (7.2)].

There was no significant impact of osilodrostat (30 mg twice daily for 12 days) on the exposure of oral contraceptives containing 0.03 mg estradiol and 0.15 mg levonorgestrel in healthy female subjects.

13 NONCLINICAL TOXICOLOGY

13.1 Carcinogenesis, Mutagenesis, and Impairment of Fertility

Carcinogenesis

Carcinogenicity studies were conducted in Wistar Han rats and CD1 mice. Hepatocellular adenomas and carcinomas occurred in male rats at ≥ 10 mg/kg and in females at 30 mg/kg (18- and 65-times the 30 mg twice daily maximum clinical dose, by AUC, respectively). Thyroid follicular adenoma/carcinoma was also observed in male rats at 30 mg/kg. Hepatocellular adenomas and carcinomas occurred in male mice at ≥ 10 mg kg (6 times the maximum clinical dose, by AUC) but not in female mice at any dose ≤ 30 mg/kg (31 times the maximum clinical dose, by AUC). These findings are likely rodent specific and considered not relevant to humans. Genetic profiling studies support activation of hepatic constitutive androstane receptors as the likely tumorigenic mechanism in rodents and is not a significant concern for human risk at clinical exposure to osilodrostat.

Genotoxicity

Genotoxicity assays conducted in vitro in bacterial systems and in vitro and in vivo in mammalian systems with and without metabolic activation indicate that there is no genotoxic risk in humans with osilodrostat.

Impairment of Fertility

In a fertility and early embryonic-development study in Wistar Han rats, doses of 50 mg/kg (118 times the 30 mg twice daily maximum clinical dose, by AUC) resulted in changes to estrous cyclicity and impaired female fertility and embryo viability. No effect on reproductive performance in females was observed at 5 mg/kg (8 times the maximum clinical dose). Fertility and reproductive performance were not affected in male rats up to 50 mg/kg (77 times the maximum clinical dose, by AUC).

14 CLINICAL STUDIES

The safety and efficacy of ISTURISA was evaluated in 2 multicenter clinical studies, Study 1 (NCT02180217) and Study 2 (NCT02697734), in adults with persistent or recurrent Cushing's disease despite pituitary surgery or de novo patients for whom surgery was not indicated or who had refused surgery. Study 1 was a 48-week study that included an 8-week, double-blind, randomized withdrawal period at Weeks 26 to 34 in the study. After Week 48, patients who maintained clinical benefit on ISTURISA could continue in a long-term extension period until the last patient reached Week 72. Study 2 was a 48-week study in which patients were randomized 2:1 to ISTURISA or placebo and treated for 12 weeks followed by a 36-week open-label treatment. After completion of week 48, patients who maintained clinical benefit on ISTURISA could continue on ISTURISA in an optional 48-week extension period.

14.1 Study 1

The safety and efficacy of ISTURISA was assessed in a 48-week, multicenter study (called the Core Period) that consisted of four study periods as follows:

- Period 1: 12-week, open-label, dose titration period
- Period 2: 12-week, open-label, maintenance treatment period
- Period 3: 8-week, double-blind, placebo-controlled, randomized withdrawal treatment period which provided the data for the primary efficacy endpoint
- Period 4: open-label treatment period of 14 to 24 weeks duration

The mean age at enrollment was 41 years; 77% of patients were female. There were 65% Caucasian, 28% Asian, 3% black, and 4% other race. Overall, 96% patients had received previous treatments for Cushing's disease prior to entering the study, of which 88% had undergone surgery. Persistence or recurrence of Cushing's disease was evidenced by the mean of three 24-hour UFC (mUFC) > 1.5× upper limit of normal (ULN). The mean mUFC (SD) at baseline was 1006 nmol/24 hr (1589) (365 mcg/24 hr), which corresponds to approximately 7 × ULN. The median mUFC at baseline was 476 nmol/24 hr (173 mcg/24 hr), which corresponds to approximately 3.5 × ULN.

Period 1 (Week 1 to 12)

One hundred thirty-seven patients received a starting dose of 2 mg ISTURISA orally twice daily that could be titrated up to a maximum of 30 mg twice daily at no greater than 2-week intervals to achieve a mUFC within the normal range. Individual dose adjustments were based on mUFC. The dose was increased if mUFC was above ULN and was reduced if mUFC was below the lower limit of normal (LLN), or if the patient had symptoms consistent with hypocortisolism and mUFC was in the lower part of the normal range.

Period 2 (Week 13 to 24)

One hundred thirty patients entered Period 2. The daily dose for patients that achieved a mUFC within the normal range in Period 1 was maintained during Period 2. Patients who did not require further dose increase, tolerated the drug, and had a mUFC ≤ ULN at Week 24 (end of Period 2) were to be considered responders and eligible to enter the Randomization Withdrawal phase (Period 3). Patients whose mUFC became elevated during Period 2 could have their dose increased further, if tolerated, up to 30 mg twice daily. These patients were considered non-responders and did not enter Period 3 but continued open-label treatment together with the patients who did not achieve normal mUFC at Week 12 and were followed for long-term safety and response to treatment.

Period 3 (Week 26 to 34)

At Week 26, 71 patients were considered responders and were randomized 1:1 to continue receiving ISTURISA (n = 36) or to switch to placebo (n = 35) for 8 weeks. Patients were stratified at randomization according to dose received at Week 24 (≤ 5 mg twice daily vs 5 mg twice daily) and history of pituitary irradiation (yes/no).

Patients were to remain on their assigned treatment and dose throughout Period 3 if mUFC were within the normal range. Blinded dose reduction or temporary discontinuation for safety or tolerability reasons were permitted. Dose increases were not permitted during Period 3. Patients with mUFC increase > 1.5 × ULN or who required a dose increase were considered non-responders and discontinued from Period 3 but allowed to receive open-label treatment during Period 4.

Period 4 (Week 26 or 34 to 48)

This period included patients who were not eligible for randomization (n = 47) at Week 26, patients who were considered non-responders during Period 3 (n = 29), and patients who were considered responders during Period 3 (n = 41). Open-label treatment with ISTURISA continued in these patients until Week 48 when patients who maintained clinical benefit on ISTURISA, as judged by the Investigator, had an option to enter an extension period of additional 24 weeks.

Efficacy Assessment

The primary efficacy endpoint of the study was the complete response status at the end of the 8-week randomized withdrawal period (Period 3). A complete responder for the primary endpoint was defined as a patient who had mUFC ≤ ULN based on central laboratory result at the end of Period 3 (Week 34), and who neither discontinued randomized treatment or the study nor had any dose increase above their Week 26 dose.

The key secondary endpoint was the complete response status at the end of Period 2 (Week 24). A complete responder for the key secondary endpoint was defined as a patient with mUFC ≤ ULN at Week 24 who did not require an increase in dose above the level established at the end of Period 1 (Week 12). Patients who were missing mUFC assessment at Week 24 were counted as non-responders for the key secondary endpoint.

Results

At the end of Period 3, the percentage of complete responders for the primary endpoint was 86% and 29% in the ISTURISA and placebo groups, respectively (Table 3). The difference in percentage of complete responders between ISTURISA and placebo groups was 57%, with 95% two-sided CI of (38%, 76%). The 95% CI were not presented by individual strata due to the small sample sizes of some of these strata.

Table 4: Percentage of Cushing's Disease Patients with Normal mUFC at End of Period 3 (8-week randomized withdrawal period) in Study 1
Primary Endpoint | ISTURISA (N = 36) n (%) | Placebo (N = 34) n (%) | Complete Responder Rate Difference (Differences in Percentages)
Complete responder rate at the end of the 8-week randomized withdrawal period (Week 34) | 31 (86) | 10 (29) | ISTURISA vs placebo 57 (38, 76)
(95% CI [CI, Confidence Interval]) | (71, 95) | (15, 47) | 2-sided p-value < 0.001

The key secondary endpoint, complete responder rate after 24 weeks of treatment with ISTURISA was achieved by 72/137 patients (52.6%) with 95% two-sided CI of (43.9, 61.1). The lower bound of this 95% CI exceeded 30%, the pre-specified threshold for statistical significance and minimum threshold for clinical benefit.

At Week 48, 91/137 patients (66%) had normal mUFC levels.

Variable decreases from baseline for blood pressure, glucose parameters, weight and weight circumference were observed at Week 48. However, because the study allowed initiation of anti-hypertensive and anti-diabetic medications and dose increases in patients already receiving such medications and the absence of a control group, the individual contribution of ISTURISA or of anti-hypertensive and anti-diabetic medication adjustments cannot be clearly established.

14.2 Study 2

The safety and efficacy of ISTURISA was assessed in a 48-week, multicenter study that consisted of two core study periods as follows:

- Period 1: 12-week, double-blind, placebo-controlled, randomized treatment period with ISTURISA or placebo.
- Period 2: 36-week, open-label, treatment period with ISTURISA.

Study 2 enrolled 74 patients with Cushing's disease, of whom 73 were treated. The mean (range) age at enrollment was 41 (19 to 67) years; 84% were female. There was 67% Caucasian, 23% Asian, 3% black, and 7% other race. Overall, 96% of patients had persistent/recurring Cushing's disease prior to entering the study, of which 88% had undergone previous surgery and 62% of patients had prior medical treatment for Cushing's disease. Persistence or recurrence of Cushing's disease was evidenced by the mean of three 24-hour UFC (mUFC) > 1.3× upper limit of normal (ULN). The mean mUFC (SD) at baseline was 432 nmol/24hr (389) (157 mcg/24 hr), which corresponds to approximately 3.1 × ULN. The median mUFC at baseline was 340 nmol/24hr (123 mcg/24 hr), which corresponds to approximately 2.5 × ULN.

Period 1 (Week 1 to 12)

Seventy-three patients received a starting dose of 2 mg twice daily ISTURISA or placebo orally twice daily that could be titrated up at approximately 3-week intervals to achieve a mUFC within the normal range, using the following dose escalation sequence: 2 mg twice daily to 5mg twice daily to 10 mg twice daily up to a maximum of 20 mg twice daily, with intermediate doses used if necessary. Individual dose adjustments were based on mUFC and other relevant data (i.e. serum cortisol, ACTH, chemistry, clinical signs and symptoms of adrenal insufficiency, vitals and study drug dose, tolerability). The dose was increased if mUFC was above ULN and was reduced if mUFC was below the lower limit of normal (LLN), or if the patients had signs and/or symptom consistent with adrenal insufficiency and mUFC was in the lower part of the normal range.

Period 2 (Week 13 to 48)

In this period, all patients who were receiving 2 mg twice daily or more during the double-blind period restarted ISTURISA at a dose of 2 mg twice daily at Week 12. Patients receiving daily dose < 2 mg twice daily during the 12-week double-blind randomized, placebo-controlled period were to continue treatment with their last dose from Period 1. During Period 2, decisions regarding dose titration of ISTURISA were made by the Investigators based on mUFC values and tolerability using the same dose escalation sequence as in the double-blind period. The maximum dose was 30 mg twice daily. Treatment with ISTURISA continued in these patients until Week 48 when patients had an option to enter an extension period of an additional 48 weeks.

Efficacy Assessment

The primary efficacy endpoint of the study was the complete response status at Week 12. A complete responder was defined as a patient who has mUFC ≤ ULN (based on central laboratory result) at Week 12 who neither discontinued during the placebo-controlled period nor had a missing mUFC assessment at Week 12.

Results

At the end of Period 1, the percentage of complete responders for the primary endpoint was 77% and 8% in the ISTURISA and placebo groups, respectively (Table 5).

Table 5: Percentage of Cushing's Disease Patients with Normal mUFC at End of Period 1 (Double-blind randomized Period) in Study 2
Primary endpoint | ISTURISA N=48 n (%) | Placebo N=25 n (%) | Complete Responder Rate Difference (Differences in Percentages) (95% CI [CI, Confidence Interval])
Complete response rate at the end of 12-weeks placebo-controlled period | 37 (77) | 2 (8) | ISTURISA vs. placebo 69 (49, 82)
(95% CI) | (62, 88) | (1, 26) | 2-sided p-value < 0.0001

16 HOW SUPPLIED/STORAGE AND HANDLING

How Supplied

ISTURISA (osilodrostat) tablets are supplied as follows:

Tablet Strength | Description | Package Configuration | NDC No.
1 mg | Pale yellow, unscored, round, biconvex with beveled edge tablet, debossed "1" on one side. | Each carton contains 6 blister packs for a total of 60 tablets. Each blister pack contains 10 tablets. | 55292-330-60
5 mg | Yellow, unscored, round, biconvex with beveled edge tablet, debossed "5" on one side. | Each carton contains 6 blister packs for a total of 60 tablets. Each blister pack contains 10 tablets. | 55292-331-60

Storage and Handling

Store at room temperature between 20°C to 25°C (68°F to 77°F); excursions permitted 15°C to 30°C (59°F to 86°F); protect from moisture.

17 PATIENT COUNSELING INFORMATION

Advise patients to read the FDA-approved patient labeling (Patient Information).

Monitoring

Instruct patients on the importance of laboratory monitoring and adhering to their return visit schedule [see Dosage and Administration (2.2, 2.3)].

Hypocortisolism

Advise patients that ISTURISA is associated with hypocortisolism-related events. Advise patients to report symptoms of hypocortisolism to their healthcare provider [see Warnings and Precautions (5.1)].

QT Prolongation

Advise patients of the signs and symptoms of QT prolongation. Advise patients to contact their healthcare provider immediately for signs or symptoms of QT prolongation.

Advise patients that an ECG will be taken before treatment and periodically thereafter. Advise patients with cardiac disease and risk factors for QT prolongation that adjustments in cardiac medications may be made and electrolyte disturbances may require correction [see Warnings and Precautions (5.2)].

Adrenal Hormone Precursors/Androgens

Advise patients that elevation of adrenal hormone precursors may occur and lead to low potassium levels, worsening of hypertension, and edema. Advise patients to report the occurrence of these symptoms to their healthcare provider.

Advise patients that elevations of androgens may occur and may lead to hirsutism, hypertrichosis, and acne (in females). Advise patients to report the occurrence of these symptoms to their healthcare provider [see Warnings and Precautions (5.3)].

Lactation

Advise females not to breastfeed during treatment with ISTURISA and for at least one week after treatment [see Use in Specific Populations (8.2)].

Manufactured for:
Recordati Rare Diseases Inc.
Bridgewater, NJ 08807 USA

© Recordati

PATIENT INFORMATION
ISTURISA® (is tur ee' sah)
(osilodrostat)
tablets, for oral use

What is the most important information I should know about ISTURISA?
ISTURISA can cause serious side effects, including:

- Low cortisol levels in your blood (hypocortisolism).

Tell your healthcare provider right away if you experience any of the following symptoms, as these may be symptoms of very low cortisol level, known as adrenal insufficiency:

- nausea
- vomiting
- tiredness (fatigue)
- low blood pressure
- problems with body salt (electrolyte) levels in your blood

- stomach (abdominal) pain
- loss of appetite
- dizziness
- low blood sugar

If you get symptoms of hypocortisolism while taking ISTURISA, your healthcare provider may change your dose or ask you to stop taking it.
Heart problem or a heart rhythm problem, such as an irregular heartbeat which could be a sign of a heart problem called QT prolongation. Call your healthcare provider right away if you have irregular heartbeats.
See "What are the possible side effects of ISTURISA?" for more information about side effects.

What is ISTURISA?
ISTURISA is a prescription medicine that is used to treat elevated levels of cortisol in the blood (endogenous hypercortisolemia) in adults with Cushing's syndrome:

- who cannot have surgery, or
- who have had surgery, but the surgery did not cure their Cushing's syndrome

It is not known if ISTURISA is safe and effective in children.

Before you take ISTURISA, tell your healthcare provider about all of your medical conditions, including if you:

- have or had heart problems, such as an irregular heartbeat, including a condition called prolonged QT syndrome (QT internal prolongation). Your healthcare provider will check the electrical signal of your heart (called an electrocardiogram) before you start taking ISTURISA, 1 week after starting ISTURISA, and as needed after that.
- have a history of low levels of potassium or magnesium in your blood.
- have liver problems.
- are pregnant or plan to become pregnant. It is not known if ISTURISA will harm your unborn baby. There are risks to the mother and unborn baby associated with active Cushing's syndrome during pregnancy.
- are breastfeeding or plan to breastfeed. It is not known if ISTURISA passes into your breast milk. You should not breastfeed if you take ISTURISA and for 1 week after stopping treatment.

Tell your healthcare provider about all the medicines you take, including prescription medicines, over-the-counter medicines, vitamins, and herbal supplements.
Especially tell your healthcare provider if you take medicines used to treat certain heart problems. Ask your healthcare provider if you are not sure whether your medicine is used to treat heart problems.

How should I take ISTURISA?

- Take ISTURISA exactly as your healthcare provider tells you. Your healthcare provider will tell you exactly how many tablets of ISTURISA to take. Do not change your dose or stop taking ISTURISA unless your healthcare provider tells you to.
- Start ISTURISA by taking 2 mg two times a day by mouth or as directed by your healthcare provider.
- After you have started treatment, your healthcare provider may change your dose, depending on how you respond to the treatment with ISTURISA.
- Take ISTURISA with or without food.
- If you miss a dose of ISTURISA, take the next dose at your regularly scheduled time.

What are the possible side effects of ISTURISA?
ISTURISA may cause serious side effects, including:

- See "What is the most important information I should know about ISTURISA?"
- Increase in other adrenal hormone levels. Your other adrenal hormones may increase when you take ISTURISA. Your healthcare provider may monitor you for the symptoms associated with these hormonal changes while you are taking ISTURISA:
  - Low potassium (hypokalemia).
  - High blood pressure (hypertension).
  - Swelling (edema) in the legs, ankles or other signs of fluid retention.
  - Excessive facial or body hair growth (hirsutism).
  - Acne (in women).

Call your healthcare provider if you have any of these side effects.
The most common side effects of ISTURISA include:

- very low cortisol levels (adrenal insufficiency)
- tiredness (fatigue)
- nausea
- headache
- swelling of the legs, ankles or other signs of fluid retention (edema)

- decreased appetite
- pain in your joints (arthralgia)
- muscle pain or soreness (myalgia)
- weakness (asthenia)
- diarrhea

These are not all of the possible side effects of ISTURISA.
Call your healthcare provider for medical advice about side effects. You may report side effects to FDA at 1-800-FDA-1088.

How should I store ISTURISA?

- Store ISTURISA at room temperature between 68°F to 77°F (20°C to 25°C).
- Keep ISTURISA dry.

Keep ISTURISA and all medicines out of the reach of children.

General information about the safe and effective use of ISTURISA.
Medicines are sometimes prescribed for purposes other than those listed in a Patient Information leaflet. Do not use ISTURISA for a condition for which it was not prescribed. Do not give ISTURISA to other people, even if they have the same symptoms you have. It may harm them. You can ask your healthcare provider or pharmacist for more information about ISTURISA that is written for healthcare professionals.

What are the ingredients in ISTURISA?
Active ingredient: osilodrostat phosphate
Inactive ingredients: colloidal silicon dioxide, croscarmellose sodium, mannitol, microcrystalline cellulose, and magnesium stearate. Tablet film-coating: hypromellose, titanium dioxide, ferric oxide (yellow), ferric oxide (red) (1 mg only), polyethylene glycol 4000, and talc.

For more information, go to www.ISTURISA.com or call 1-888-575-8344.
Manufactured for: Recordati Rare Diseases Inc., Bridgewater, NJ 08807 USA
© Recordati

This Patient Information has been approved by the U.S. Food and Drug Administration.

Revised: 11/2025

PRINCIPAL DISPLAY PANEL - 1 mg Blister Pack Carton

NDC 55292-330-60

Isturisa® 1 mg
(osilodrostat)
tablets

Rx only

Each tablet contains 1 mg osilodrostat (as osilodrostat phosphate).

60 film-coated tablets

RECORDATI
RARE DISEASES

PRINCIPAL DISPLAY PANEL - 5 mg Blister Pack Carton

NDC 55292-331-60

Isturisa® 5 mg
(osilodrostat)
tablets

Rx only

Each tablet contains 5 mg osilodrostat (as osilodrostat phosphate).

60 film-coated tablets

RECORDATI
RARE DISEASES

PRINCIPAL DISPLAY PANEL - 1 mg Blister Pack Carton

NDC 55292-320-60

Isturisa® 1 mg
(osilodrostat)
tablets

Rx only

Each tablet contains 1 mg osilodrostat (as osilodrostat phosphate).

60 film-coated tablets

RECORDATI
RARE DISEASES

PRINCIPAL DISPLAY PANEL - 5 mg Blister Pack Carton

NDC 55292-321-60

Isturisa® 5 mg
(osilodrostat)
tablets

Rx only

Each tablet contains 5 mg osilodrostat (as osilodrostat phosphate).

60 film-coated tablets

RECORDATI
RARE DISEASES

PRINCIPAL DISPLAY PANEL - 10 mg Blister Pack Carton

NDC 55292-322-60

Isturisa® 10 mg
(osilodrostat)
tablets

Rx only

Each tablet contains 10 mg osilodrostat (as osilodrostat phosphate).

60 film-coated tablets

RECORDATI
RARE DISEASES